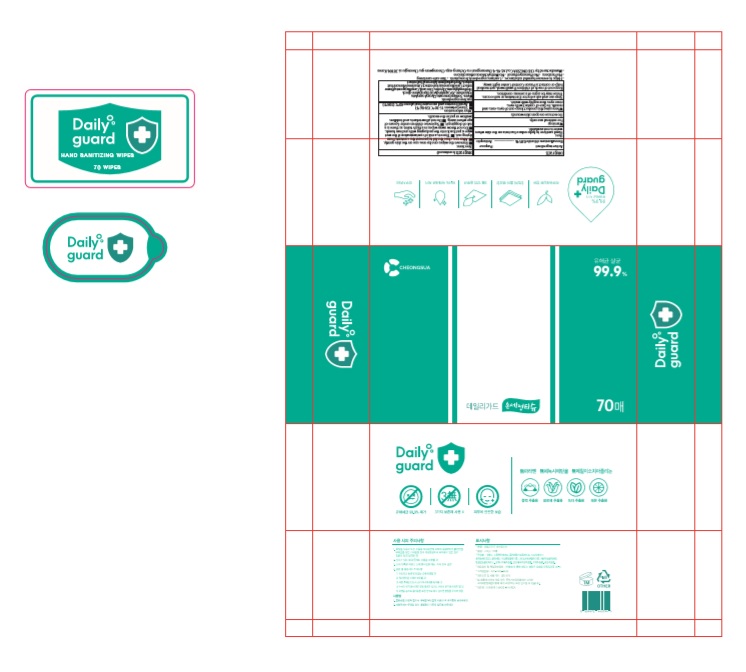 DRUG LABEL: Daily guard HAND SANITIZING WIPES
NDC: 78964-005 | Form: CLOTH
Manufacturer: CHEONGSUA
Category: otc | Type: HUMAN OTC DRUG LABEL
Date: 20200609

ACTIVE INGREDIENTS: BENZALKONIUM CHLORIDE 0.0005 1/1 1
INACTIVE INGREDIENTS: DIPROPYLENE GLYCOL; WATER; SODIUM BENZOATE; GLYCERYL CAPRYLATE; GLYCERIN; CAPRYLYL GLYCOL; ETHYLHEXYLGLYCERIN; POLYSORBATE 20; CITRIC ACID MONOHYDRATE; CAMELLIA JAPONICA FLOWER; GREEN TEA LEAF; LEMON; ALOE VERA LEAF

Daily guard HAND SANITIZING WIPES | 70 WIPES | 70 WIPES IN 1 PACKET | 78964-005-70